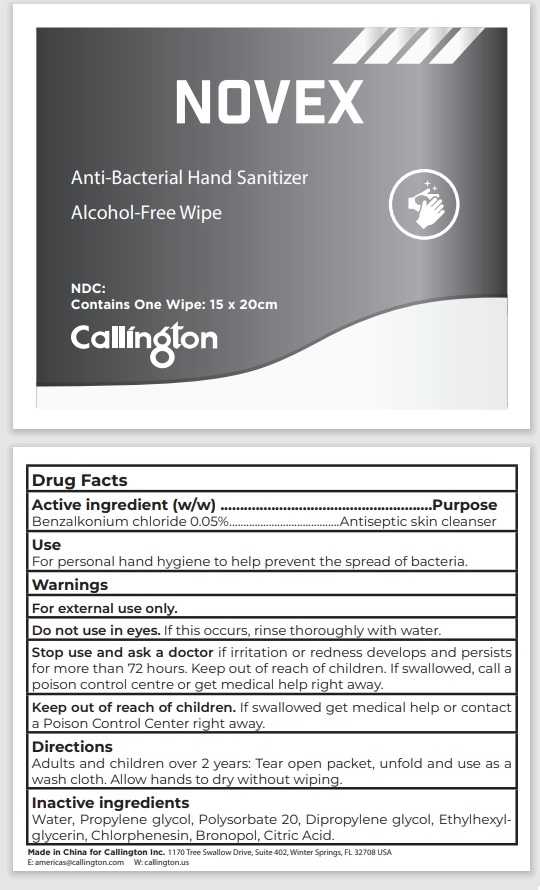 DRUG LABEL: Novex Anti-Bacterial Hand Sanitizer Wipe
NDC: 71734-118 | Form: SWAB
Manufacturer: JIANGMEN SHUIZIRUN SANITARY ARTICLES CO., LTD.
Category: otc | Type: HUMAN OTC DRUG LABEL
Date: 20240710

ACTIVE INGREDIENTS: BENZALKONIUM CHLORIDE 0.05 g/100 g
INACTIVE INGREDIENTS: WATER; PROPYLENE GLYCOL; POLYSORBATE 20; DIPROPYLENE GLYCOL; CHLORPHENESIN; BRONOPOL

Anti-Bacterial Hand Sanitizer Wipe

DRUG FACTS

Active Ingredient

Benzalkonium Chloride .......... 0.05 %

Purpose

Antiseptic

Uses:

For personal hand hygiene to help prevent the spread of bacteria.

Warnings

For external use only.

Do not use in eyes. If this occurs, rinse thoroughly with water.

Stop use and ask a doctor if irritation or redness develops and persists for more than 72 hours.

Keep out of reach of children. If swallowed, get medical help or contact a Poison Control Center right away.

Directions

Adults and children over 2 years: Tear open packet, unfold and use as a wash cloth. Allow hands to dry without wiping.

Inactive Ingredients:

Water, Propylene glycol, Polysorbate 20, Dipropylene glycol, Ethylhexyl_x0002_glycerin, Chlorphenesin, Bronopol, Citric Acid.